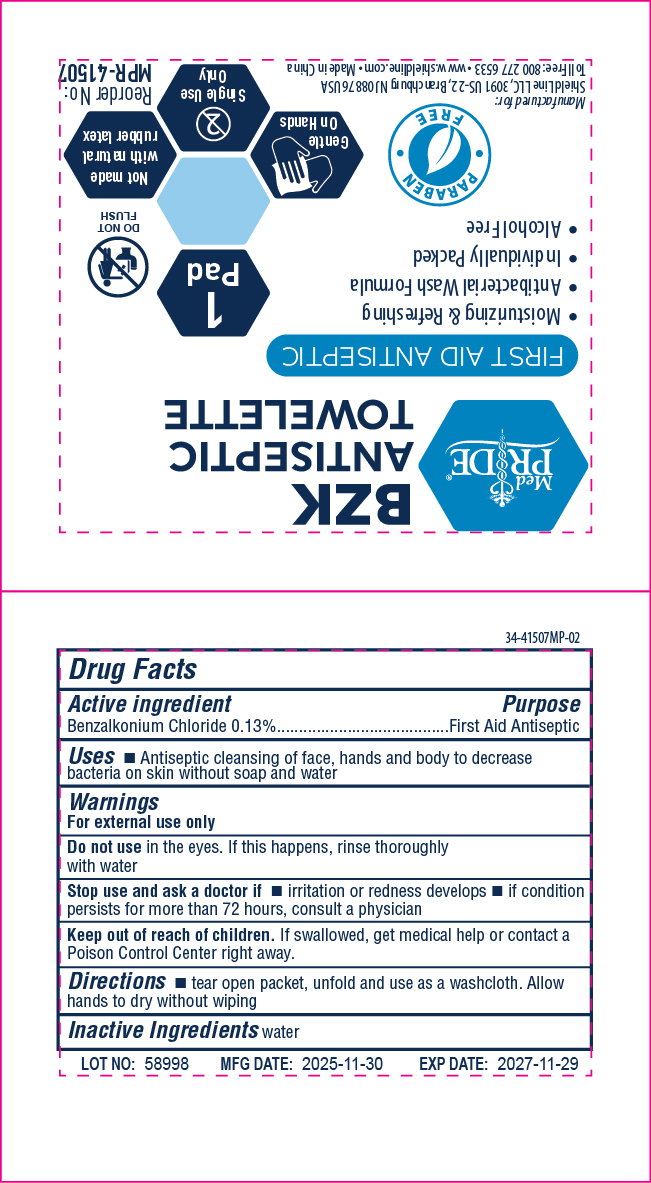 DRUG LABEL: MedPride
NDC: 52410-4150 | Form: CLOTH
Manufacturer: Shield Line LLC
Category: otc | Type: HUMAN OTC DRUG LABEL
Date: 20260227

ACTIVE INGREDIENTS: BENZALKONIUM CHLORIDE 0.133 g/1 1
INACTIVE INGREDIENTS: WATER

Drug Facts

Active Ingredient

Benzalkonium Chloride 0.133%

Purpose

Antiseptic

Uses

For topical antimicrobial use

Warnings

For external use only
■ flammable, keep away from fire or flame

Do not use

■ with electrocautery procedures ■ in the eyes, if contact occurs, flush eyes with water

Stop use and ask a doctor if

■if irritation and redness develops. if condition persist consult your health practitioner.

Keep out of reach of children.If swallowed contact a doctor or Poison Control Center right away.

Directions

■wipe the required site vigorously and discard

Other information

■ store at room temperature 15C-30C (59F-86F)

Inactive Ingredients

purified water, camphor